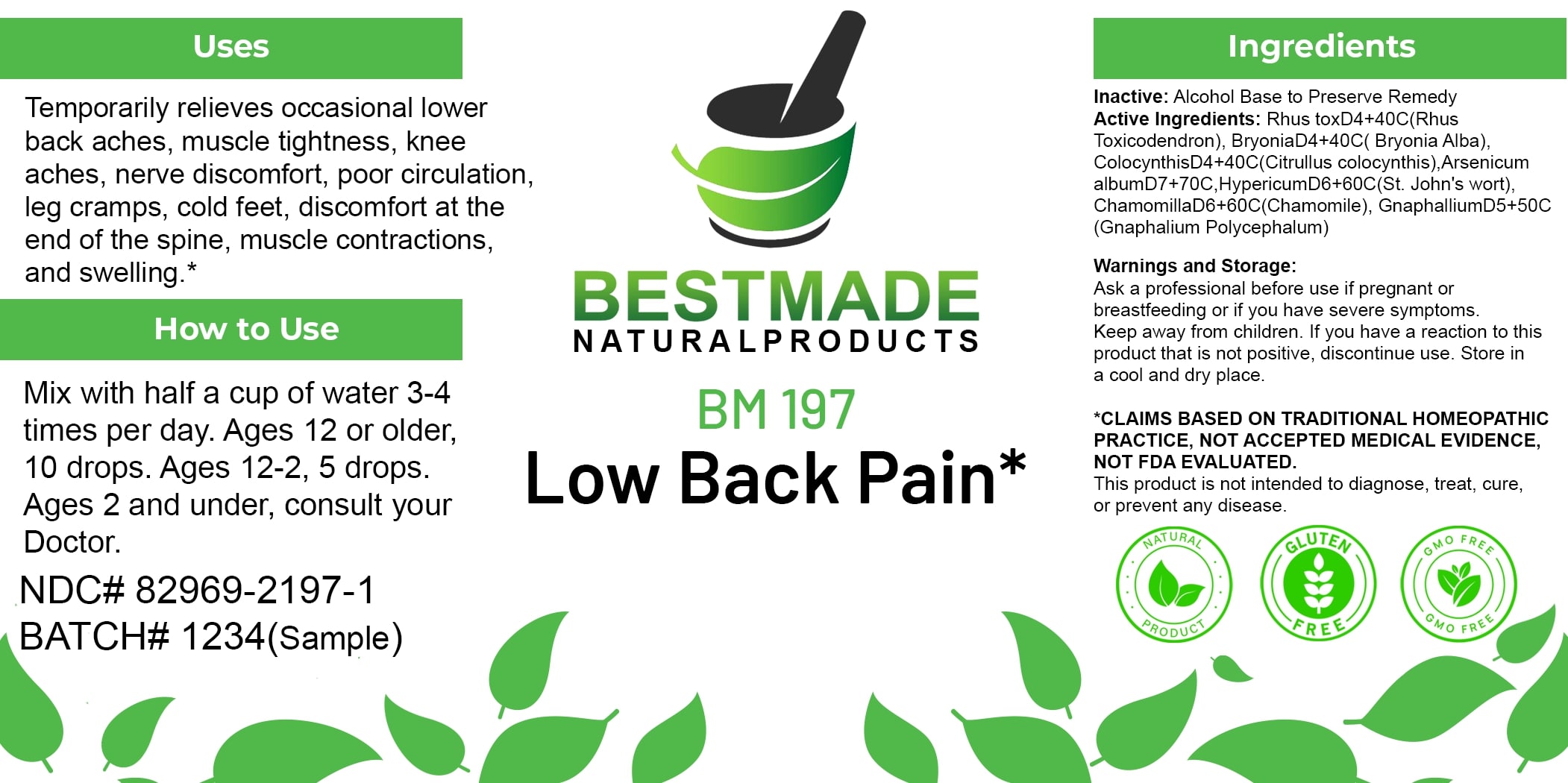 DRUG LABEL: Bestmade Natural Products BM197
NDC: 82969-2197 | Form: LIQUID
Manufacturer: Bestmade Natural Products
Category: homeopathic | Type: HUMAN OTC DRUG LABEL
Date: 20250225

ACTIVE INGREDIENTS: HYPERICUM PERFORATUM 30 [hp_C]/30 [hp_C]; MATRICARIA CHAMOMILLA 30 [hp_C]/30 [hp_C]; ARSENIC TRIOXIDE 30 [hp_C]/30 [hp_C]; BRYONIA ALBA ROOT 30 [hp_C]/30 [hp_C]; TOXICODENDRON PUBESCENS LEAF 30 [hp_C]/30 [hp_C]; CITRULLUS COLOCYNTHIS FRUIT PULP 30 [hp_C]/30 [hp_C]; PSEUDOGNAPHALIUM OBTUSIFOLIUM 30 [hp_C]/30 [hp_C]
INACTIVE INGREDIENTS: ALCOHOL 30 [hp_C]/30 [hp_C]

BM197

DOSAGE AND ADMINISTRATION

How to Use

Mix with half a cup of water 3-4 times per day. Ages 12 or older, 10 drops. Ages 12-2, 5 drops. Ages 2 and under, consult your Doctor.

Uses

Temporarily relieves occasional lower back aches, muscle tightness, knee aches, nerve discomfort, poor circulation, leg cramps, cold feet, discomfort at the end of the spine, muscle contractions, and swelling.*

*CLAIMS BASED ON TRADITIONAL HOMEOPATHIC PRACTICE, NOT ACCEPTED MEDICAL EVIDENCE. NOT FDA EVALUATED.

This product is not intended to diagnose, treat, cure, or prevent any disease.

INACTIVE INGREDIENT

Ingredients

Inactive: Alcohol Base to Preserve Remedy

ACTIVE INGREDIENT

Active Ingredients: Rhus toxD4+40C(Rhus Toxicodendron), BryoniaD4+40C(Bryonia Alba), ColocynthisD4+40C(Citrullus colocynthis), Arsenicum albumD7+70C, HypericumD6+60C(St. John's wort), ChamomillaD6+60C(Chamomile), GnaphaliumD5+50C (Gnaphalium Polycephalum)

Warnings and Storage:

Ask a professional before use if pregnant or breastfeeding or if you have severe symptoms. Keep away from children. If you have a reaction to this product that is not positive, discontinue use. Store in a cool and dry place.

*CLAIMS BASED ON TRADITIONAL HOMEOPATHIC PRACTICE, NOT ACCEPTED MEDICAL EVIDENCE. NOT FDA EVALUATED.

This product is not intended to diagnose, treat, cure, or prevent any disease.

KEEP OUT OF REACH OF CHILDREN

Warnings and Storage:

Ask a professional before use if pregnant or breastfeeding or if you have severe symptoms. Keep away from children. If you have a reaction to this product that is not positive, discontinue use. Store in a cool and dry place.

Uses

Temporarily relieves occasional lower back aches, muscle tightness, knee aches, nerve discomfort, poor circulation, leg cramps, cold feet, discomfort at the end of the spine, muscle contractions, and swelling.*

*CLAIMS BASED ON TRADITIONAL HOMEOPATHIC PRACTICE, NOT ACCEPTED MEDICAL EVIDENCE. NOT FDA EVALUATED.

This product is not intended to diagnose, treat, cure, or prevent any disease.

Entire package label